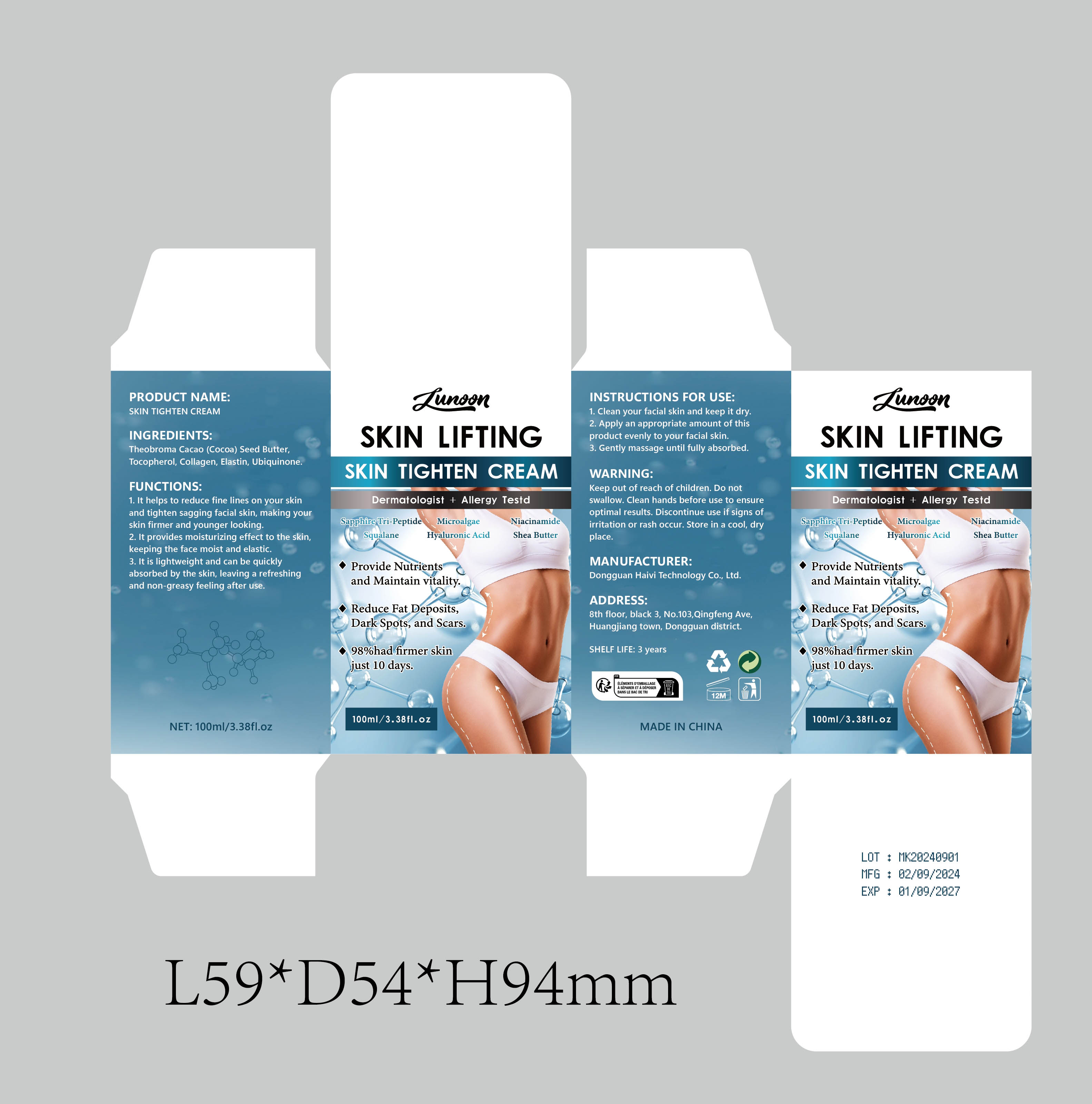 DRUG LABEL: SKIN TIGHTEN Cream
NDC: 84732-019 | Form: CREAM
Manufacturer: Dongguan Haiyi Technology Co.,Ltd.
Category: otc | Type: HUMAN OTC DRUG LABEL
Date: 20240926

ACTIVE INGREDIENTS: COCOA BUTTER 1 mg/100 mL
INACTIVE INGREDIENTS: TOCOPHEROL; ELASTIN (HUMAN); PENICILLOYL POLYLYSINE; UBIDECARENONE

Active ingredient

Theobroma cacao (Cocoa) seed Butter

Inactive ingredient

Tocopherol, collagen, Elastin, Ubiquinone.

Purpose section

1. lt helps to reduce fine lines on your skinand tighten sagging facial skin, making yourskin firmer and younger looking.

2. lt provides moisturizing effect to the skin,keeping the face moist and elastic.

3. It is lightweight and can be quicklyabsorbed by the skin, leaving a refreshingand non-greasy feeling after use.

Warning

Keep out of reach of children. Do not swallow, Clean hands before use to ensure optimal results. Discontinue use if signs of irritation or rash occur. Store in a cool, dryplace.

stop use

This product may cause allergic reactions in asmall number of people.
lf youexperience any discomfort,please stop using it immediately.

not use

Not suitable for use by children, pregnantor breastfeeding people.

OUT OF CHILDREN

KEEP THE PRODUCT OUT OF REACH OF CHILDREN to

HOW TO USE

1. Clean your facial skin and keep it dry

2. Apply an appropriate amount of thisproduct evenly to your facial skin.

3. Gently massage until fully absorbed.

Dosage

take an appropriateamount,Use 2-3 times a week